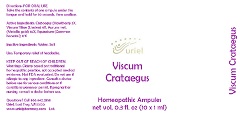 DRUG LABEL: Viscum Crataegus
NDC: 48951-9072 | Form: LIQUID
Manufacturer: Uriel Pharmacy Inc.
Category: homeopathic | Type: HUMAN OTC DRUG LABEL
Date: 20190612

ACTIVE INGREDIENTS: HAWTHORN LEAF WITH FLOWER 3 [hp_X]/1 mL; VISCUM ALBUM FRUITING TOP 4 [hp_X]/1 mL; GOLD 10 [hp_X]/1 mL; EQUISETUM ARVENSE TOP 17 [hp_X]/1 mL
INACTIVE INGREDIENTS: WATER; SODIUM CHLORIDE

Viscum Crataegus

INDICATIONS AND USAGE

Directions: FOR ORAL USE.

DOSAGE AND ADMINISTRATION

Take the contents of one ampule under the tongue and hold for 30 seconds, then swallow.

ACTIVE INGREDIENT

Active Ingredients: Crataegus (Hawthorn) 3X, Viscum Tiliae (Linden) 4X, Aurum met. (Metallic gold) 10X, Equisetum (Common horsetail) 17X

Inactive Ingredients: Water, Salt

PURPOSE

Use: Temporary relief of headache.

KEEP OUT OF REACH OF CHILDREN.

WARNINGS

Warnings: Claims based on traditional homeopathic practice, not accepted medical evidence. Not FDA evaluated. Do not use if allergic to any ingredient. Consult a doctor before use for serious conditions or if conditions worsen or persist. If pregnant or nursing, consult a doctor before use.

Questions? Call 866.642.2858
Uriel, East Troy, WI 53120
www.urielpharmacy.com